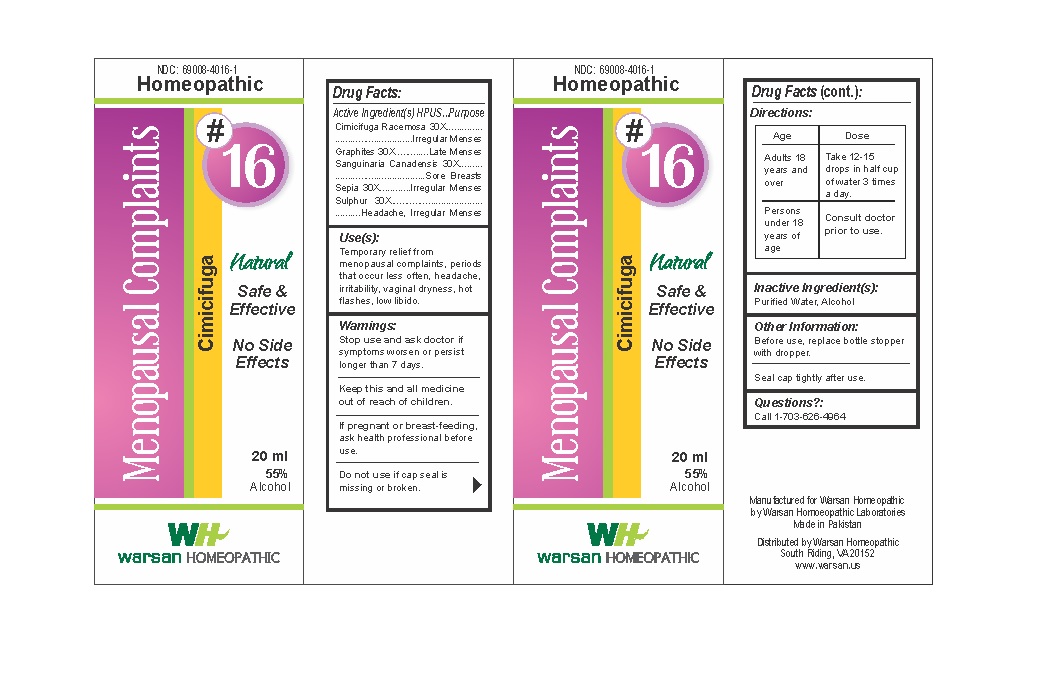 DRUG LABEL: Combination Remedy 16 - Menopausal Complaints
NDC: 69008-4016 | Form: SOLUTION/ DROPS
Manufacturer: Warsan Homoeopathic Laboratories
Category: homeopathic | Type: HUMAN OTC DRUG LABEL
Date: 20171225

ACTIVE INGREDIENTS: SEPIA OFFICINALIS JUICE 30 [hp_X]/1 mL; GRAPHITE 30 [hp_X]/1 mL; SANGUINARIA CANADENSIS ROOT 30 [hp_X]/1 mL; BLACK COHOSH 30 [hp_X]/1 mL; SULFUR 30 [hp_X]/1 mL
INACTIVE INGREDIENTS: ALCOHOL; WATER

Stop use and ask doctor if symptoms worsen or persist longer than 7 days.

If pregnant or breast-feeding, ask health professional before use.

Do not use if tamper evident seal is missing or broken.

Keep out of reach of children.

ACTIVE INGREDIENT

Cimicifuga Racemosa 30X

Graphites 30X

Sanguinaria Canadensis 30X

Sepia 30X

Sulphur 30X

PURPOSE

Temporary relief from menopausal complaints, periods that occur less often, headache, irritability, vaginal dryness, hot flashes, low libido.

INACTIVE INGREDIENT

Purified Water

Alcohol

DOSAGE AND ADMINISTRATION

Adults 18 years and older: Take 10-15 drops in half cup of water 3 times a day.

Not inteded for use by persons under 18.

INDICATIONS AND USAGE

Temporary relief from menopausal complaints, periods that occur less often, headache, irritability, vaginal dryness, hot flashes, low libido.